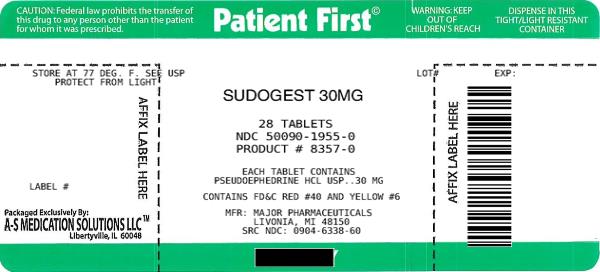 DRUG LABEL: SudoGest
NDC: 50090-1955 | Form: TABLET, COATED
Manufacturer: A-S Medication Solutions
Category: otc | Type: HUMAN OTC DRUG LABEL
Date: 20200118

ACTIVE INGREDIENTS: PSEUDOEPHEDRINE HYDROCHLORIDE 30 mg/1 1
INACTIVE INGREDIENTS: ACACIA; CALCIUM SULFATE ANHYDROUS; CARNAUBA WAX; SILICON DIOXIDE; STARCH, CORN; D&C RED NO. 27; D&C YELLOW NO. 10; FD&C RED NO. 40; FD&C YELLOW NO. 6; FERROSOFERRIC OXIDE; FERRIC OXIDE RED; FERRIC OXIDE YELLOW; KAOLIN; MICROCRYSTALLINE CELLULOSE; POLYETHYLENE GLYCOL 400; SODIUM STARCH GLYCOLATE TYPE A POTATO; STEARIC ACID; SUCROSE; TALC; TITANIUM DIOXIDE

SudoGest 30 mg Tablets

Active Ingredient

In each tablet Pseudoephedrine HCl 30 mg

Purpose

Nasal Decongestant

Keep out of reach of children. In case of overdose, get medical help or contact a Poison Control Center right away

Indications and Usage

Temporarily relieves nasal congestion due to the common cold, hay fever or other upper respiratory allergies, and nasal congestion associated with sinusitis

Temporarily relieves sinus congestion and pressure

Warnings

WARNINGS: Do not use if you are now taking a prescription monoamine oxidase inhibitor (MAOI) (certain drugs for depression, psychiatric or emotional conditions, or Parkinson’s disease), or for 2 weeks after stopping the MAOI drug. If you do not know if your prescription drug contains an MAOI, ask a doctor or pharmacist before taking this product.

Dosage and Administration

Directions – take every 4-6 hours -Do not take more than 4 does in 24 hours

Adults and children 12 years and over – 2 tablets

Children 6 to under 12 years – 1 tablet

Children under 6 years – do not use

Inactive Ingredients

INACTIVE INGREDIENTS: acacia, calcium sulfate, carnauba Wax. colloidal silicon dioxide, corn starch, D-C red no. 27, D-C yellow no.10, FD-C red no.40, FD-C yellow no 6, iron oxide black, iron oxide red, iron oxide yellow (iron oxide ochre) Kaolin, microcrystalline cellulose, polyethylene glycol (PEG) 400, , pregelatinized starch, sodium starch glycolate, stearic acid, sugar, talc, titanium dioxide

Questions or Comments?

1-800-616-2471

Storage

Store at 25ºC (77ºF). Excursions permitted between 15º-30ºC (59º-86ºF).

Protect from light.

HOW SUPPLIED

Product: 50090-1955

NDC: 50090-1955-0 28 TABLET, COATED in a BOTTLE